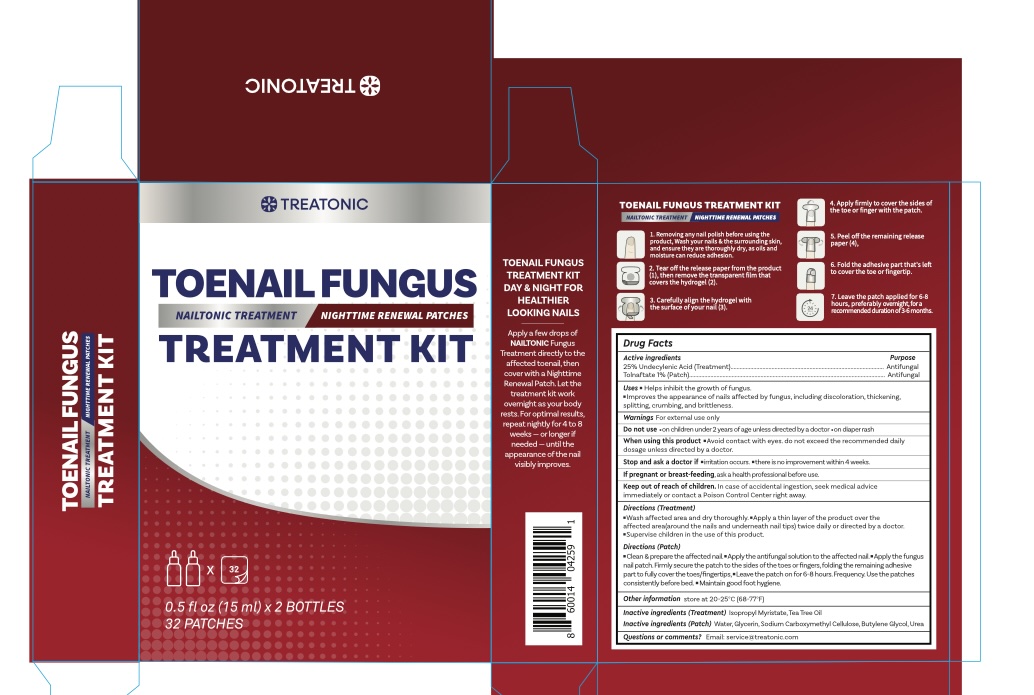 DRUG LABEL: Treatonic Toenail Fungus Treatment Kit
NDC: 85569-010 | Form: KIT | Route: TOPICAL
Manufacturer: 100 KARMA INC
Category: otc | Type: HUMAN OTC DRUG LABEL
Date: 20260301

ACTIVE INGREDIENTS: UNDECYLENIC ACID 25 g/100 mL; TOLNAFTATE 1 g/100 1
INACTIVE INGREDIENTS: ISOPROPYL MYRISTATE; TEA TREE OIL; WATER; GLYCERIN; CARBOXYMETHYLCELLULOSE SODIUM; UREA; BUTYLENE GLYCOL

Update-85569-010-01

ACTIVE INGREDIENT

25% Undecylenic Acid
1% Tolnaftate

PURPOSE

Anti-fungal

INDICATIONS AND USAGE

- Helps Inhibit the growth of fungus.
- Improves the appearance of nails affected by fungus, including discoloration, thickening, splitting, crumbing, and brittleness.

WARNINGS

For external use only

DO NOT USE

- on children under 2 years of age unless directed by a doctor.
- on diaper rash

when using this product:
avoid contact with eyes. Do not exceed the recommended daily dosge unless directed by a doctor.

Stop use and ask a doctor if

- irritation occurs
- this is no improvement within 4 weeks.

PREGNANCY OR BREAST FEEDING

If pregnant or breast feeding, ask a health professional before use.

KEEP OUT OF REACH OF CHILDREN

In case of accidental ingestion, seek medical advice immediately or contact a poison control center right away.

DOSAGE AND ADMINISTRATION

Directions (Treatment)

- Wash affected area and dry thoroughly.
- Apply a thin layer of the product over the affected area (around the nails and underneath nail tips) twice daily or directed by a doctor.
- Supervise children in the use of this product.

Directions (Patch)

- Clean & prepare the affected nail.
- Apply the antifungal solution to the affected nail.
- Apply the fungus nail patch. Firmly secure the patch to the sides of the toes or fingers, folding the remaining adhesive part to fully cover the toes/fingertips.
- Leave the patch on for 6-8 hours. Frequency: Use the patches consistently before bed.
- Maintain good foot hygiene.

OTHER SAFETY INFORMATION

Store at 20-25°C (68-77°F)

INACTIVE INGREDIENT

(Treatment) Isopropyl Myristate, Tea Tree Oil

(Patch) Water, Glycerin, Sodium Carboxymethyl Cellulose, Butylene Glycol, Urea

QUESTIONS

Email: service@treatonic.com